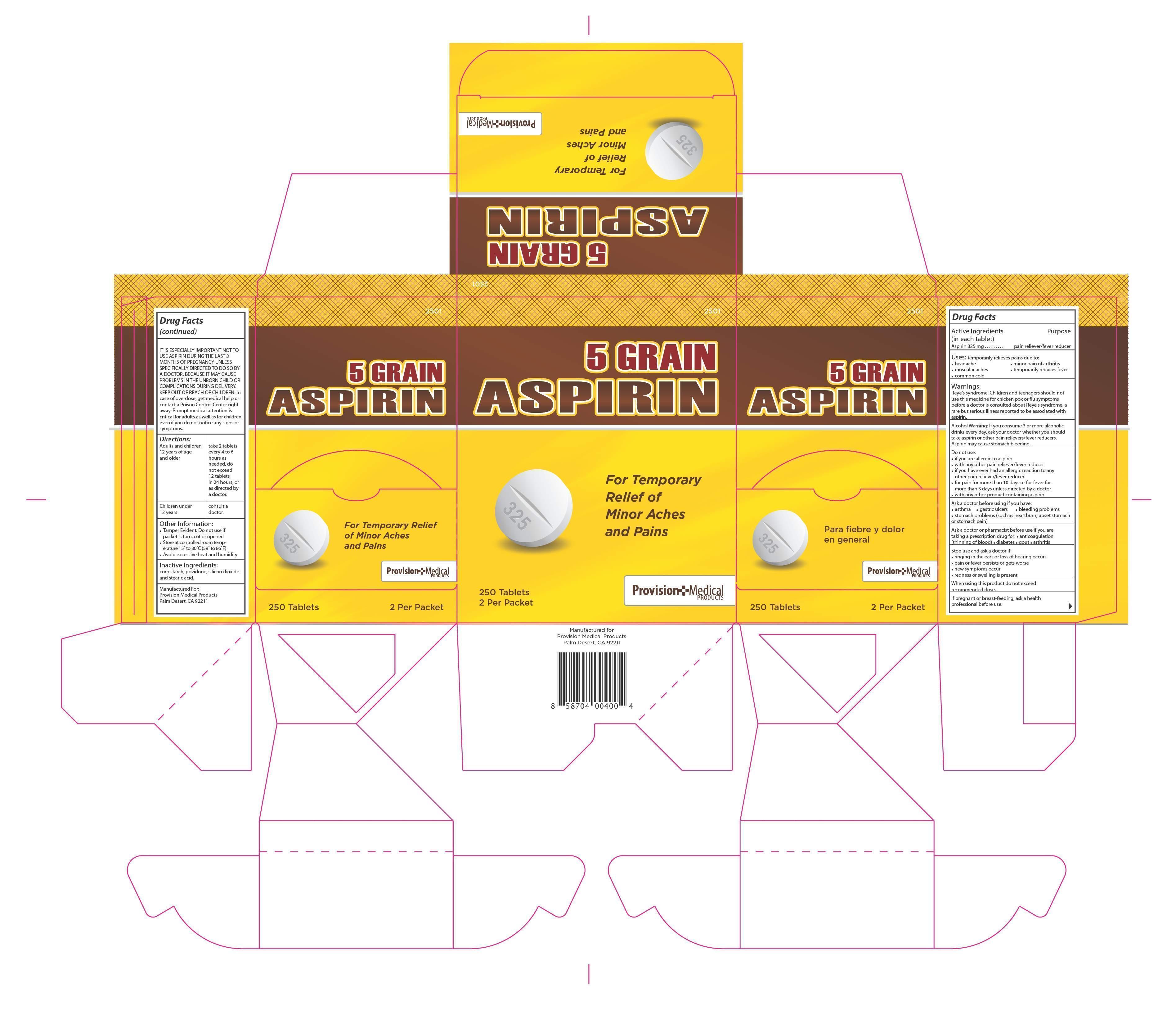 DRUG LABEL: Aspirin 5 grain
NDC: 69103-2501 | Form: TABLET
Manufacturer: Provision Medical Products
Category: otc | Type: HUMAN OTC DRUG LABEL
Date: 20191001

ACTIVE INGREDIENTS: ASPIRIN 325 mg/1 1
INACTIVE INGREDIENTS: POVIDONE K30; SILICON DIOXIDE; STARCH, CORN; STEARIC ACID

Uses:

temporarily relieves pains due to:•headache • minor pain of arthritis•muscular aches • temporarily reduces fever•common cold

If pregnant or breast-feeding, ask a health

professional before use.

IT IS ESPECIALLY IMPORTANT NOT TO

USE ASPIRIN DURING THE LAST 3

MONTHS OF PREGNANCY UNLESS

SPECIFICALLY DIRECTED TO DO SO BY

A DOCTOR, BECAUSE IT MAY CAUSE

PROBLEMS IN THE UNBORN CHILD OR

COMPLICATIONS DURING DELIVERY.

KEEP OUT OF REACH OF CHILDREN. In

case of overdose, get medical help or

contact a Poison Control Center right

away. Prompt medical attention is

critical for adults as well as for children

even if you do not notice any signs or

symptoms.

Warnings:

Reye's syndrome: Children and teenagers should not

use this medicine for chicken pox or -u symptoms

before a doctor is consulted about Reye's syndrome, a

rare but serious illness reported to be associated with

aspirin.

Alcohol Warning: If you consume 3 or more alcoholic

drinks every day, ask your doctor whether you should

take aspirin or other pain relievers/fever reducers.

Aspirin may cause stomach bleeding.

Do not use:

•

if you are allergic to aspirin

•

with any other pain reliever/fever reducer

•

if you have ever had an allergic reaction to any

other pain reliever/fever reducer

•

for pain for more than 10 days or for fever for

more than 3 days unless directed by a doctor

•

with any other product containing aspirin

Ask a doctor before using if you have:

•

asthma • gastric ulcers • bleeding problems

•

stomach problems (such as heartburn, upset stomach

or stomach pain)

Ask a doctor or pharmacist before use if you are

taking a prescription drug for:

• anticoagulation

(thinning of blood)

• diabetes • gout • arthritis

Stop use and ask a doctor if:

•

ringing in the ears or loss of hearing occurs

•

pain or fever persists or gets worse

•

new symptoms occur

•

redness or swelling is present

When using this product do not exceed

recommended dose

Directions:

Adults and children 12 years of age and older take 2 tablets every 4 to 6hours as

needed, do not exceed 12 tablets in 24 hours, or as directed by

a doctor.

Children under 12 years consult a

doctor.

Do not use more than directed

Inactive Ingredients:

corn starch, povidone, silicon dioxide

and stearic acid.

ACTIVE INGREDIENT-ASPIRIN 325 MG

PURPOSE

PAIN RELIEVER/FEVER REDUCER